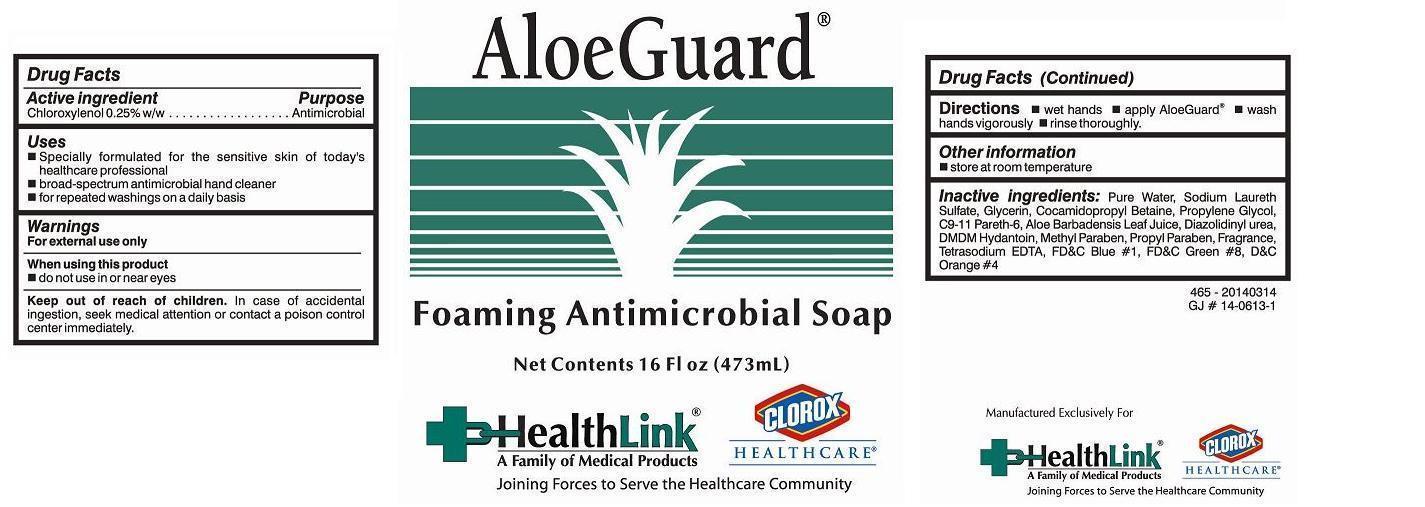 DRUG LABEL: FOAMING ALOEGUARD ANTIMICROBIAL
NDC: 63843-465 | Form: SOAP
Manufacturer: HealthLink
Category: otc | Type: HUMAN OTC DRUG LABEL
Date: 20140630

ACTIVE INGREDIENTS: CHLOROXYLENOL 2.5 g/1000 mL
INACTIVE INGREDIENTS: WATER; SODIUM LAURETH SULFATE; GLYCERIN; COCAMIDOPROPYL BETAINE; PROPYLENE GLYCOL; C9-11 PARETH-6; ALOE VERA LEAF; DIAZOLIDINYL UREA; DMDM HYDANTOIN; METHYLPARABEN; PROPYLPARABEN; EDETATE SODIUM

Drug Facts Active ingredient

Chloroxylenol 0.25% w/w

Purpose

Antimicrobial

Keep out of reach of children

In case of accidental ingestion, seek medical attention or contact a poison control center immediately.

Uses

 Specially formulated for the sensitive skin of today's healthcare professional
 broad-spectrum antimicrobial hand cleaner
 for repeated washings on a daily basis

Warnings

For external use only

When using this product

 do not use in or near eyes

Keep out of reach of children. In case of accidental ingestion, seek medical attention or contact a poison control center immediately.

Directions

 wet hands  apply AloeGuard  wash hands vigorously  rinse thoroughly.

Other information

 store at room temperature

Inactive ingredients:

Water, Sodium Laureth Sulfate, Glycerin, Cocamidopropyl Betaine, Proplyene Glycol, C9-11 Pareth-6, Aloe Barbadensis Leaf Juice, Diazolidinyl Urea, DMDM Hydantoin, Methyl Paraben, Propyl Paraben, Fragrance, Tetrasodium EDTA, FD&C Blue #1, FD&C Green #8, D&C Orange #4.